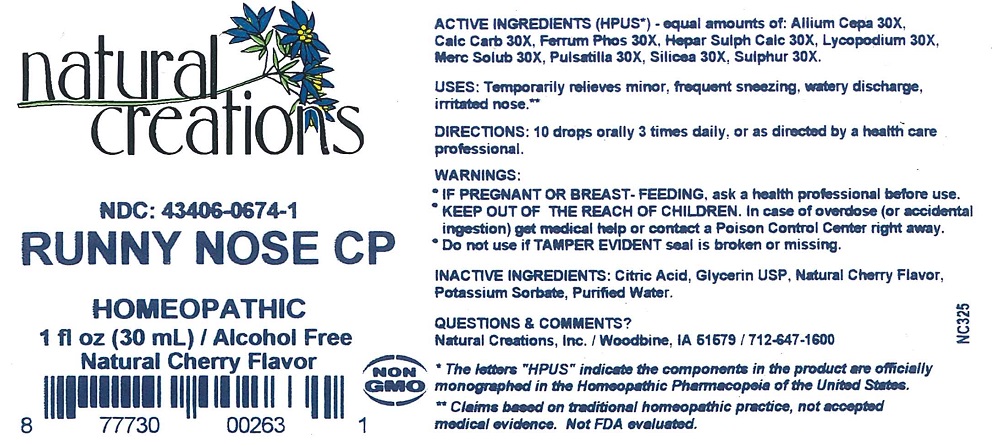 DRUG LABEL: Runny Nose CP
NDC: 43406-0674 | Form: LIQUID
Manufacturer: Natural Creations, Inc
Category: homeopathic | Type: HUMAN OTC DRUG LABEL
Date: 20181221

ACTIVE INGREDIENTS: ONION 30 [hp_X]/1 mL; OYSTER SHELL CALCIUM CARBONATE, CRUDE 30 [hp_X]/1 mL; FERROSOFERRIC PHOSPHATE 30 [hp_X]/1 mL; CALCIUM SULFIDE 30 [hp_X]/1 mL; LYCOPODIUM CLAVATUM SPORE 30 [hp_X]/1 mL; MERCURIUS SOLUBILIS 30 [hp_X]/1 mL; PULSATILLA VULGARIS WHOLE 30 [hp_X]/1 mL; SILICON DIOXIDE 30 [hp_X]/1 mL; SULFUR 30 [hp_X]/1 mL
INACTIVE INGREDIENTS: CITRIC ACID MONOHYDRATE; GLYCERIN; POTASSIUM SORBATE; WATER

Runny Nose CP

ACTIVE INGREDIENT

ACTIVE INGREDIENTS (HPUS*) - equal amounts of: Allium Cepa 30X, Calc Carb 30X, Ferrum Phos 30X, Hepar Sulph Calc 30X, Lycopodium 30X, Merc Solub 30X, Pulsatilla 30X, Silicea 30X, Sulphur 30x

INDICATIONS AND USAGE

USES: Temporarily relieves minor, frequent sneezingm watery discharge, irritated nose.**

PURPOSE

USES: Temporarily relieves minor, frequent sneezingm watery discharge, irritated nose.**

DOSAGE AND ADMINISTRATION

DIRECTIONS: Adults & children above 12 years: 10 drops orally 3 times daily, or as directed by a health care professional.

KEEP OUT OF REACH OF CHILDREN

KEEP OUT OF THE REACH OF CHILDREN. In case of overdose (or accidental ingestion) get medical help or contact a Poison Control Center right away.

WARNINGS:

- Consult a physician for use in children under 12 years of age.
- IF PREGNANT OR BREAST-FEEDING, ask a health care professional before use.
- KEEP OUT OF THE REACH OF CHILDREN. In case of overdose (or accidental ingestion) get medical help or contact a Poison Control Center right away.
- Do not use if TAMPER EVIDENT seal is broken or missing.

INACTIVE INGREDIENT

INACTIVE INGREDIENTS: Citric Acid, Glycerin USP, Natural Cherry Flavor, Potassium Sorbate, Purified Water

QUESTIONS & COMMENTS?

Natural Creations, Inc. / Woodbine, IA 51579 / 712-647-1600

REFERENCES

*The letters "HPUS" indicate the components in the product are officially monographed in the Homeopathic Pharmacopeia of the United States.

**Claims based on traditional homeopathic practice, not accepted medical evidence. Not FDA evaluated.

PACKAGE LABEL

NDC:43406-0674-1

Runny Nose CP

HOMEOPATHIC

1 fl oz (30mL) / Alcohol Free